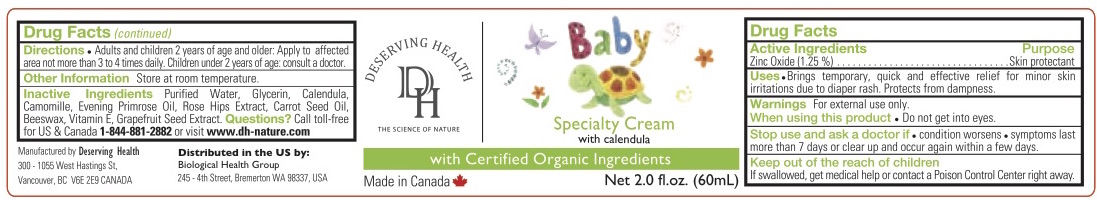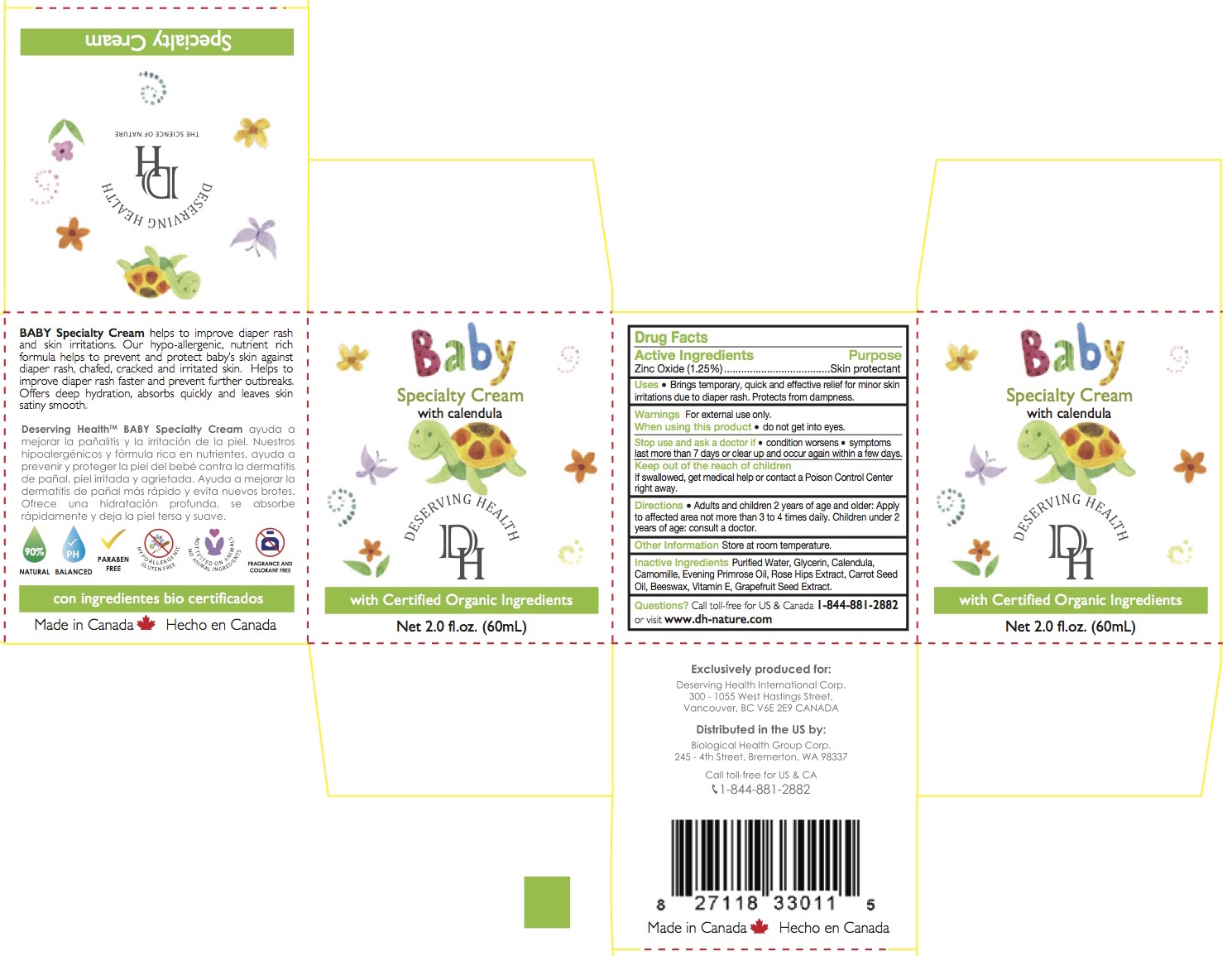 DRUG LABEL: Baby Specialty Cream
NDC: 69711-900 | Form: CREAM
Manufacturer: Deserving Health
Category: otc | Type: HUMAN OTC DRUG LABEL
Date: 20200220

ACTIVE INGREDIENTS: ZINC OXIDE 0.75 g/60 mL
INACTIVE INGREDIENTS: YELLOW WAX; CITRUS PARADISI SEED; CARROT SEED OIL; ALPHA-TOCOPHEROL; WATER; CALENDULA OFFICINALIS FLOWER; CHAMOMILE; EVENING PRIMROSE OIL; ROSA CANINA FRUIT OIL; GLYCERIN

ACTIVE INGREDIENT

ZINC OXIDE............................1.25%.............Skin Protectant

ASK DOCTOR

If swalled, get medical healp or contact a Poison Control Center right away.

Stop use and ask a doctor if

condition worsens

symptoms last more than 7 days or clear up and occur again with a few days

Keep out of the reach of children

Use

Brings temporary, quick and and effective relief for minor skin irritations due to diaper rash. Protects from dampness.

Inactive Ingredients

Purified Water, Glycerin, Calendula Oil, Camomile Oil, Evening Primrose Oil, Rose Hips Extract, Carrot Seed Oil, Beeswax, Vitamine E, Grapefruit extract.

Stop use and ask a doctor if

condition worsens

symptoms last more than 7 days or clear up and occur again within a few days

Warning

For external use only

WHEN USING

do not get into eyes